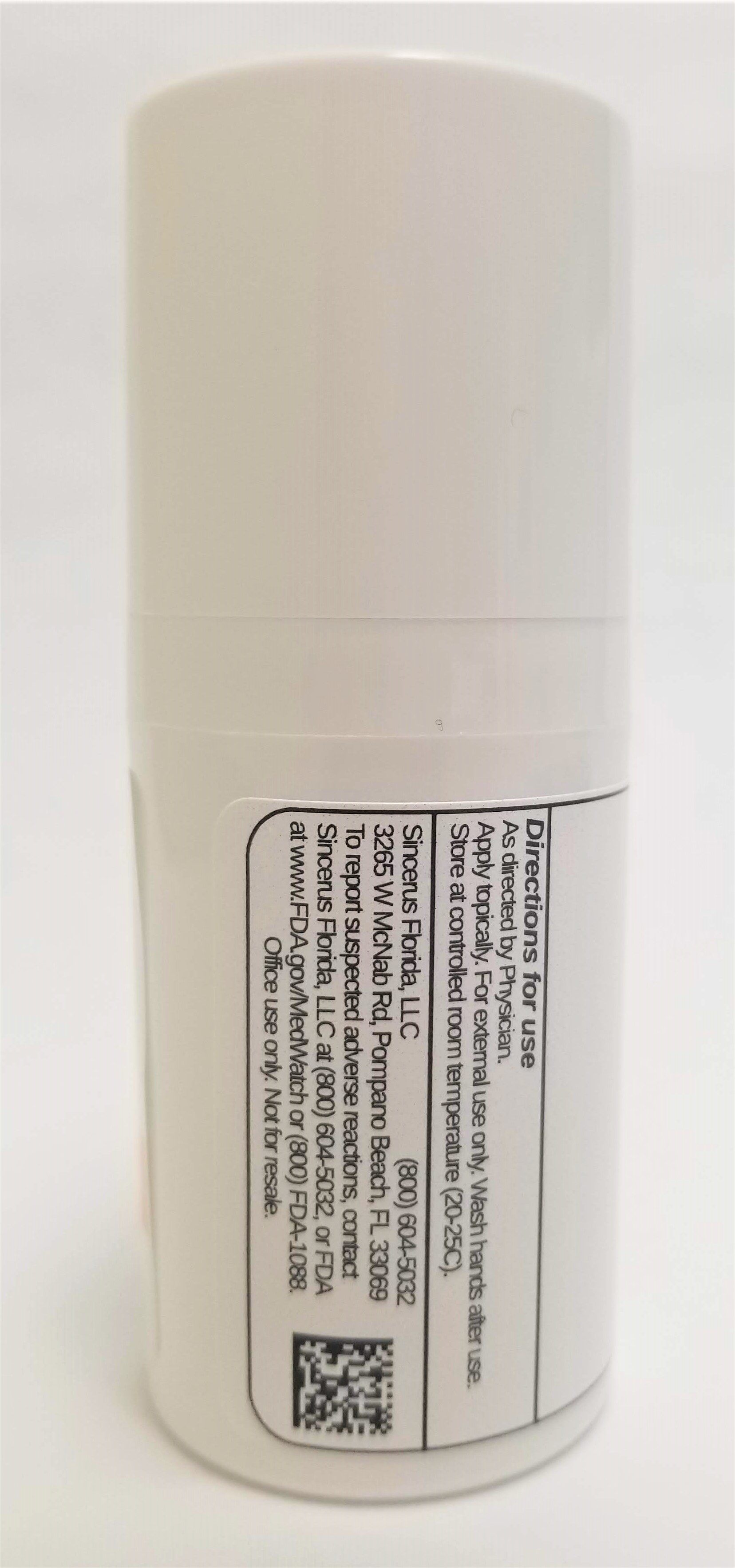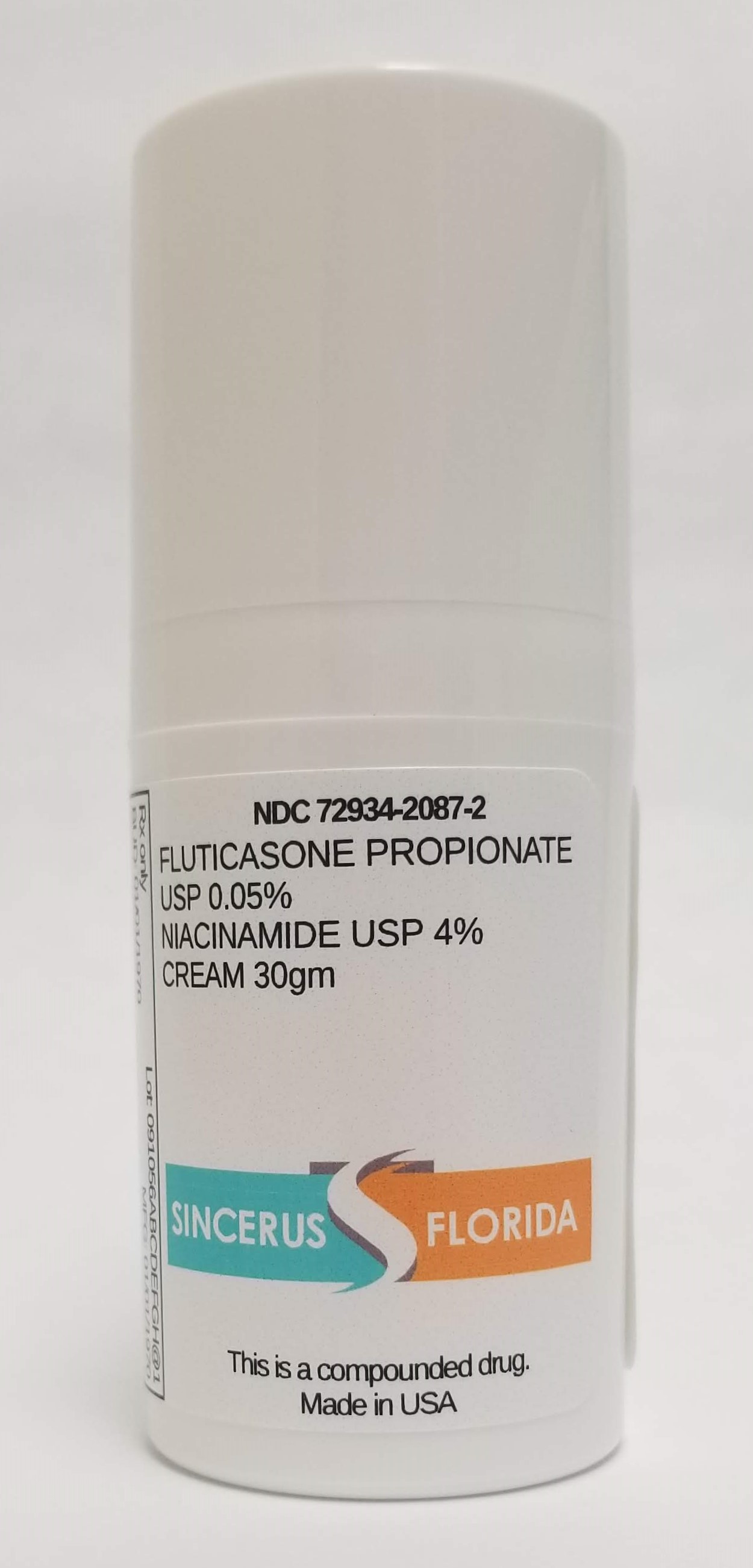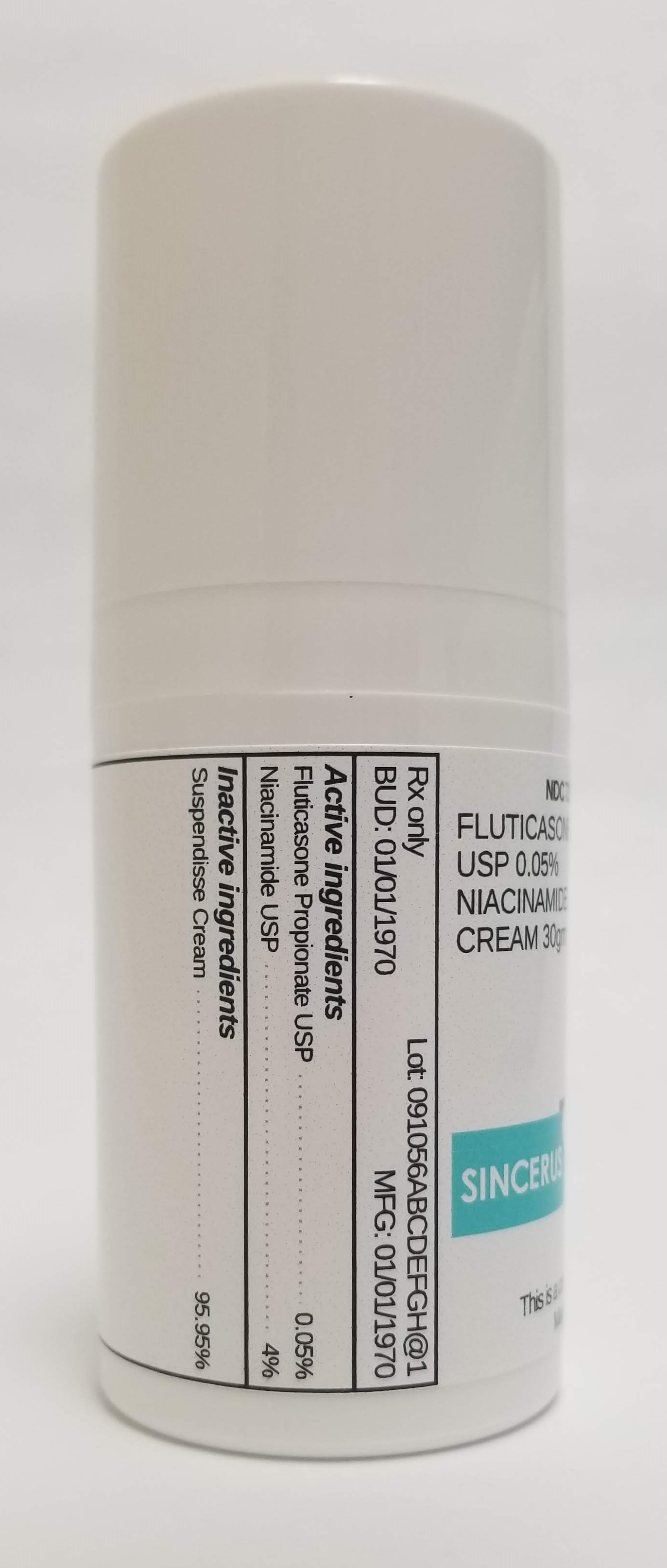 DRUG LABEL: FLUTICASONE PROPIONATE 0.05% / NIACINAMIDE 4%
NDC: 72934-2087 | Form: CREAM
Manufacturer: Sincerus Florida, LLC
Category: prescription | Type: HUMAN PRESCRIPTION DRUG LABEL
Date: 20190513

ACTIVE INGREDIENTS: FLUTICASONE PROPIONATE 0.05 g/100 g; NIACINAMIDE 4 g/100 g

FLUTICASONE PROPIONATE 0.05% / NIACINAMIDE 4%